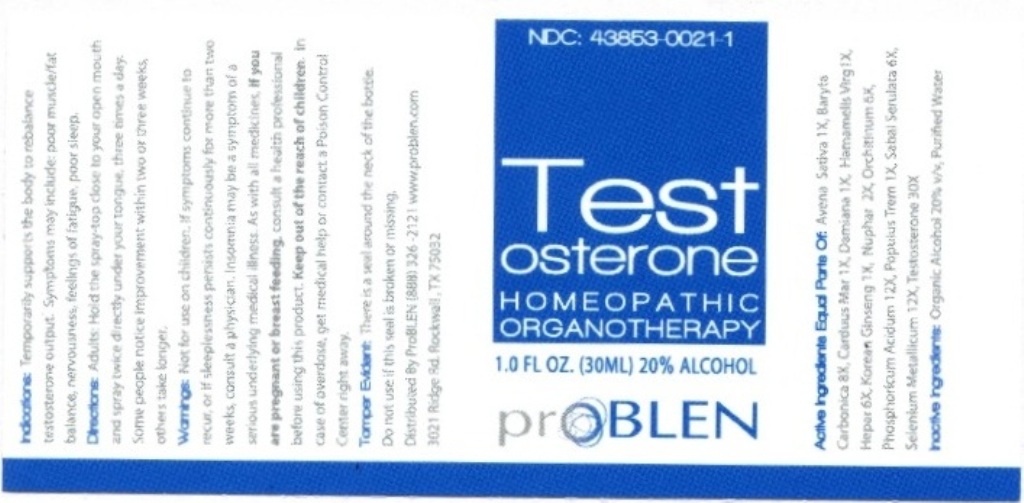 DRUG LABEL: Testosterone
NDC: 43853-0021 | Form: LIQUID
Manufacturer: ProBlen
Category: homeopathic | Type: HUMAN OTC DRUG LABEL
Date: 20201005
DEA Schedule: CIII

ACTIVE INGREDIENTS: AVENA SATIVA FLOWERING TOP 1 [hp_X]/30 mL; BARIUM CARBONATE 8 [hp_X]/30 mL; MILK THISTLE 1 [hp_X]/30 mL; TURNERA DIFFUSA LEAFY TWIG 1 [hp_X]/30 mL; HAMAMELIS VIRGINIANA ROOT BARK/STEM BARK 1 [hp_X]/30 mL; PORK LIVER 6 [hp_X]/30 mL; ASIAN GINSENG 1 [hp_X]/30 mL; NUPHAR LUTEA ROOT 2 [hp_X]/30 mL; SUS SCROFA TESTICLE 6 [hp_X]/30 mL; PHOSPHORIC ACID 12 [hp_X]/30 mL; POPULUS TREMULOIDES LEAF 1 [hp_X]/30 mL; SAW PALMETTO 6 [hp_X]/30 mL; SELENIUM 12 [hp_X]/30 mL; TESTOSTERONE 30 [hp_X]/30 mL
INACTIVE INGREDIENTS: ALCOHOL; WATER

ProBLEN Testosterone

ACTIVE INGREDIENT

Active Ingredients Equal Parts Of: Avena Sativa 1X, Baryta Carbonica 8X, Carduus Mar 1X, Damiana 1X, Hamamelis Virg 1X, Hepar 6X, Korean Ginseng 1X, Nuphar 2X, Orchitinum 6X, Phosphoricum Acidum 12X, Populus Trem 1X, Sabal Serulata 6X, Selenium Metallicum 12X, Testosterone 30X.

INDICATIONS AND USAGE

Indications: Temporarily supports the body to rebalancet tesosterone output. Symptoms may include: poor muscle/fat balance, nervousness, feelings of fatigue, poor sleep.

WARNINGS

Warnings: Not for use on children. If symptoms continue to recur, or if sleeplessness persists continuously for more than two weeks, consult a physician. Insomnia may be a symptom of a serious underlying medical illness. As with all medicines, if you are pregnant or breast feeding, consult a health professional before using this product. In case of overdose, get medical help or contact a Poison Control Center right away.

- Keep out of reach of children.

DOSAGE AND ADMINISTRATION

Directions: Adults: Hold the spray-top close to your open mouth and spray twice directly under your tongue, three times a day. Some people notice improvement within two or three weeks, others take longer.

OTHER SAFETY INFORMATION

Tamper Evident: There is a seal around the neck of the bottle. Do not use if seal is broken or missing.

INACTIVE INGREDIENT

Inactive Ingredients: Organic Alcohol 20% v/v, Purified Water

QUESTIONS

Distributed By ProBlen (888) 326-2121 www. problen.com

3021 Ridge Rd. Rockwall, TX 75032

PACKAGE LABEL

NDC: 43853-0021-1

Testosterone

HOMEOPATHIC ORGANOTHERAPY

1.0 FL OZ. (30ML) 20% ALCOHOL

ProBlen

PURPOSE

Temporarily supports the body to rebalancet tesosterone output.